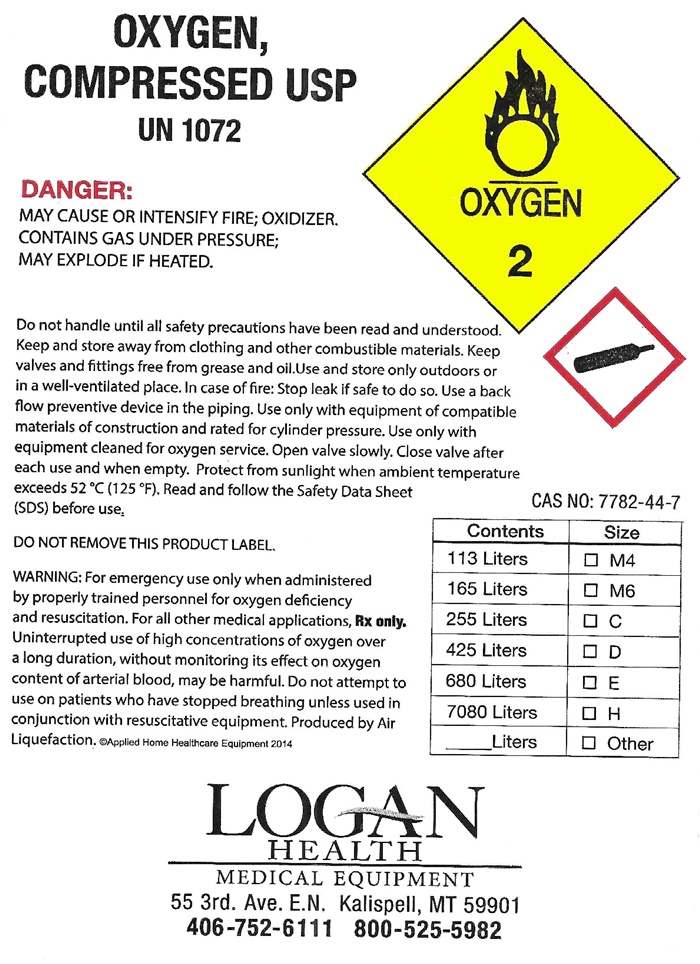 DRUG LABEL: OXYGEN
NDC: 60696-1234 | Form: GAS
Manufacturer: Logan Health
Category: prescription | Type: HUMAN PRESCRIPTION DRUG LABEL
Date: 20250219

ACTIVE INGREDIENTS: OXYGEN 99 L/100 L

OXYGEN COMPRESSED LABEL

OXYGEN, COMPRESSED USP UN1072 OXYGEN 2

DANGER; MAY CAUSE OR INTENSIFY FIRE; OXIDIZER, CONTAINS GAS UNDER PRESSURE; MAY EXPLODE IF HEATED.

Do not handle until all safety precautions have been read and understood. Keep and store away from clothing and other combustive material. Keep valves and fittings free from grease and oil. Use and store only outdoors or in a well-ventilated place. In case of fire: Stop leak if safe to do so. Use a back flow preventive device in the piping. Use only with equipment of compatible materials of construction and rated for cylinder pressure. Use only with equipment cleaned for oxygen service. Open valve slowly. Close valve after each use and when empty. Protect from sunlight when ambient temperature exceeds 52° C (125° F). Read and follow the Safety Data Sheet (SDS) before use.

DO NOT REMOVE THIS PRODUCT LABEL

WARNING: For emergency use only when administered by properly trained personnel for oxygen deficiency and resuscitation. For all other medical applications. Rx only. Uninterrupted use of high concentrations of oxygen over a long duration without monitoring its effect on oxygen content of arterial blood, may be harmful. Do not attempt to use on patients who have stopped breathing unless used in conjunction with resuscitative equipment. Produced by Air Liquefaction. © Applied Home Healthcare Equipment 2014

CAS 7782-44-7

Contents Size

113 Liters __M4

165 Liters __M6

255 Liters __ C

425 Liters __ D

680 Liters __ E

7080 Liters __ H

___ Liters __ Other

LOGAN

HEALTH

MEDICAL EQUIPMENT

55 3rd Avenue E.N. Kalispell, MT 59901

406-752-6111 800-525-5982